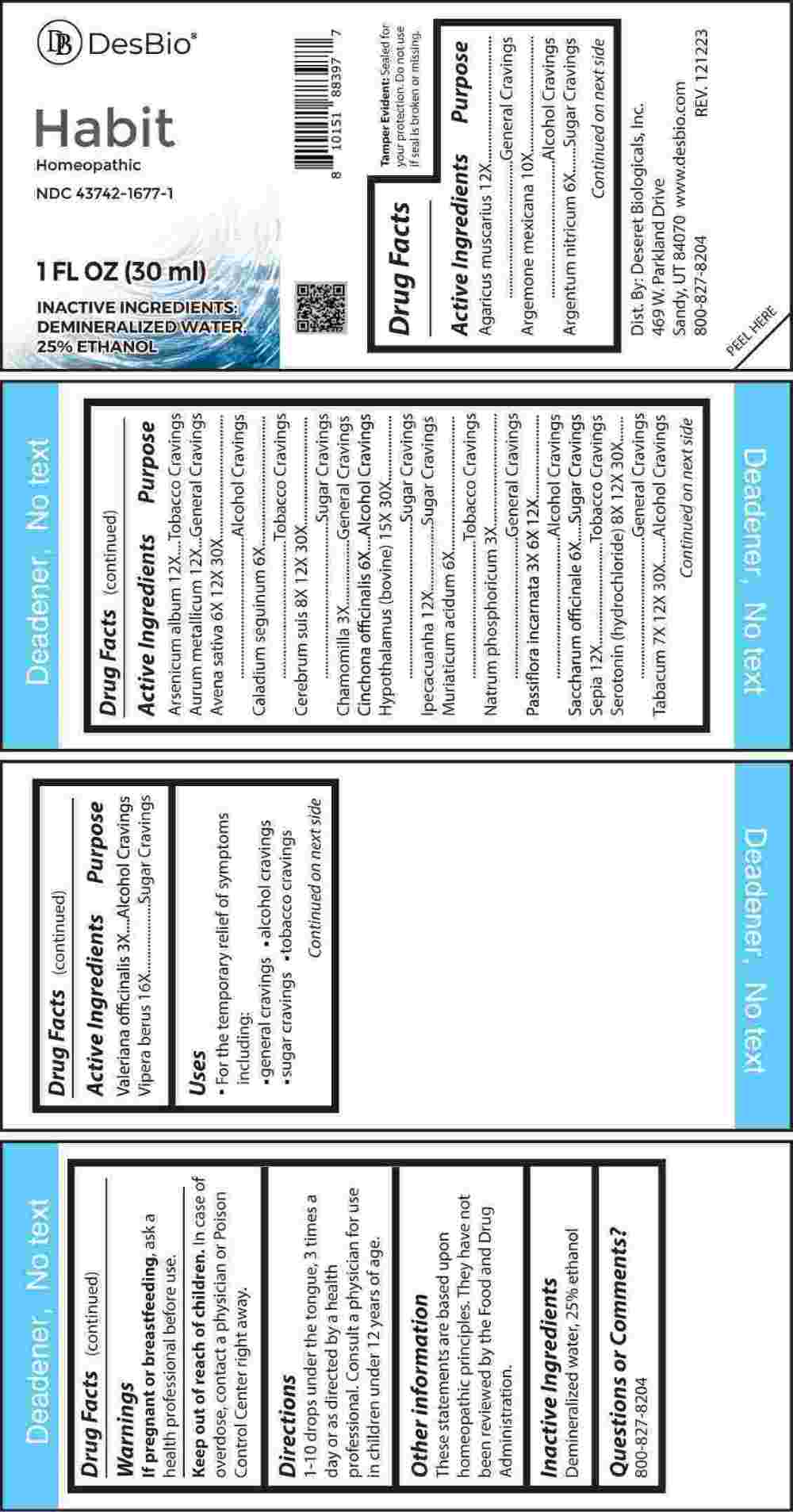 DRUG LABEL: Habit
NDC: 43742-1677 | Form: LIQUID
Manufacturer: Deseret Biologicals, Inc.
Category: homeopathic | Type: HUMAN OTC DRUG LABEL
Date: 20240315

ACTIVE INGREDIENTS: MATRICARIA CHAMOMILLA WHOLE 3 [hp_X]/1 mL; SODIUM PHOSPHATE, DIBASIC, HEPTAHYDRATE 3 [hp_X]/1 mL; VALERIAN 3 [hp_X]/1 mL; PASSIFLORA INCARNATA FLOWERING TOP 3 [hp_X]/1 mL; SILVER NITRATE 6 [hp_X]/1 mL; DIEFFENBACHIA SEGUINE WHOLE 6 [hp_X]/1 mL; CINCHONA OFFICINALIS BARK 6 [hp_X]/1 mL; HYDROCHLORIC ACID 6 [hp_X]/1 mL; SUCROSE 6 [hp_X]/1 mL; AVENA SATIVA FLOWERING TOP 6 [hp_X]/1 mL; TOBACCO LEAF 7 [hp_X]/1 mL; SUS SCROFA CEREBRUM 8 [hp_X]/1 mL; SEROTONIN HYDROCHLORIDE 8 [hp_X]/1 mL; ARGEMONE MEXICANA 10 [hp_X]/1 mL; AMANITA MUSCARIA FRUITING BODY 12 [hp_X]/1 mL; ARSENIC TRIOXIDE 12 [hp_X]/1 mL; GOLD 12 [hp_X]/1 mL; IPECAC 12 [hp_X]/1 mL; SEPIA OFFICINALIS JUICE 12 [hp_X]/1 mL; BOS TAURUS HYPOTHALAMUS 15 [hp_X]/1 mL; VIPERA BERUS VENOM 16 [hp_X]/1 mL
INACTIVE INGREDIENTS: WATER; ALCOHOL

DRUG FACTS:

ACTIVE INGREDIENT:

Agaricus Muscarius 12X, Argemone Mexicana 10X, Argentum Nitricum 6X, Arsenicum Album 12X, Aurum Metallicum 12X, Avena Sativa 6X, 12X, 30X, Caladium Seguinum 6X, Cerebrum Suis 8X, 12X, 30X, Chamomilla 3X, Cinchona Officinalis 6X, Hypothalamus (Bovine) 15X, 30X, Ipecacuanha 12X, Muriaticum Acidum 6X, Natrum Phosphoricum 3X, Passiflora Incarnata 3X, 6X, 12X, Saccharum Officinale 6X, Sepia 12X, Serotonin (Hydrochloride) 8X, 12X, 30X, Tabacum 7X, 12X, 30X, Valeriana Officinalis 3X, Vipera Berus 16X.

PURPOSE:

Agaricus Muscarius – General Cravings, Argemone Mexicana – Alcohol Cravings, Argentum Nitricum – Sugar Cravings, Arsenicum Album – Tobacco Cravings, Aurum Metallicum – General Cravings, Avena Sativa – Alcohol Cravings, Caladium Seguinum – Tobacco Cravings, Cerebrum Suis – Sugar Cravings, Chamomilla – General Cravings, Cinchona Officinalis – Alcohol Cravings, Hypothalamus (Bovine) – Sugar Cravings, Ipecacuanha – Sugar Cravings, Muriaticum Acidum – Tobacco Cravings, Natrum Phosphoricum – General Cravings, Passiflora Incarnata – Alcohol Cravings, Saccharum Officinale – Sugar Cravings, Sepia – Tobacco Cravings, Serotonin (Hydrochloride) – General Cravings, Tabacum – Alcohol Cravings, Valeriana Officinalis – Alcohol Cravings, Vipera Berus – Sugar Cravings

USES:

• For the temporary relief of symptoms including:

• general cravings • alcohol cravings • sugar cravings • tobacco cravings

These statements are based upon homeopathic principles. They have not been reviewed by the Food and Drug Administration.

WARNINGS:

If pregnant or breast-feeding, ask a health professional before use.

Keep out of reach of children. In case of overdose, contact a physician or Poison Control Center right away.

Tamper Evident: Sealed for your protection. Do not use if seal is broken or missing.

KEEP OUT OF REACH OF CHILDREN:

In case of overdose, contact a physician or Poison Control Center right away.

DIRECTIONS:

1-10 drops under the tongue, 3 times a day or as directed by a health professional. Consult a physician for use in children under 12 years of age.

INACTIVE INGREDIENTS:

Demineralized water, 25% ethanol

QUESTIONS:

Dist. By: Deseret Biologicals, Inc.

469 W. Parkland Drive

Sandy, UT 84070

www.desbio.com

800-827-8204

PACKAGE LABEL DISPLAY:

Des Bio

Habit

Homeopathic

NDC 43742-1677-1

1 FL OZ (30ml)